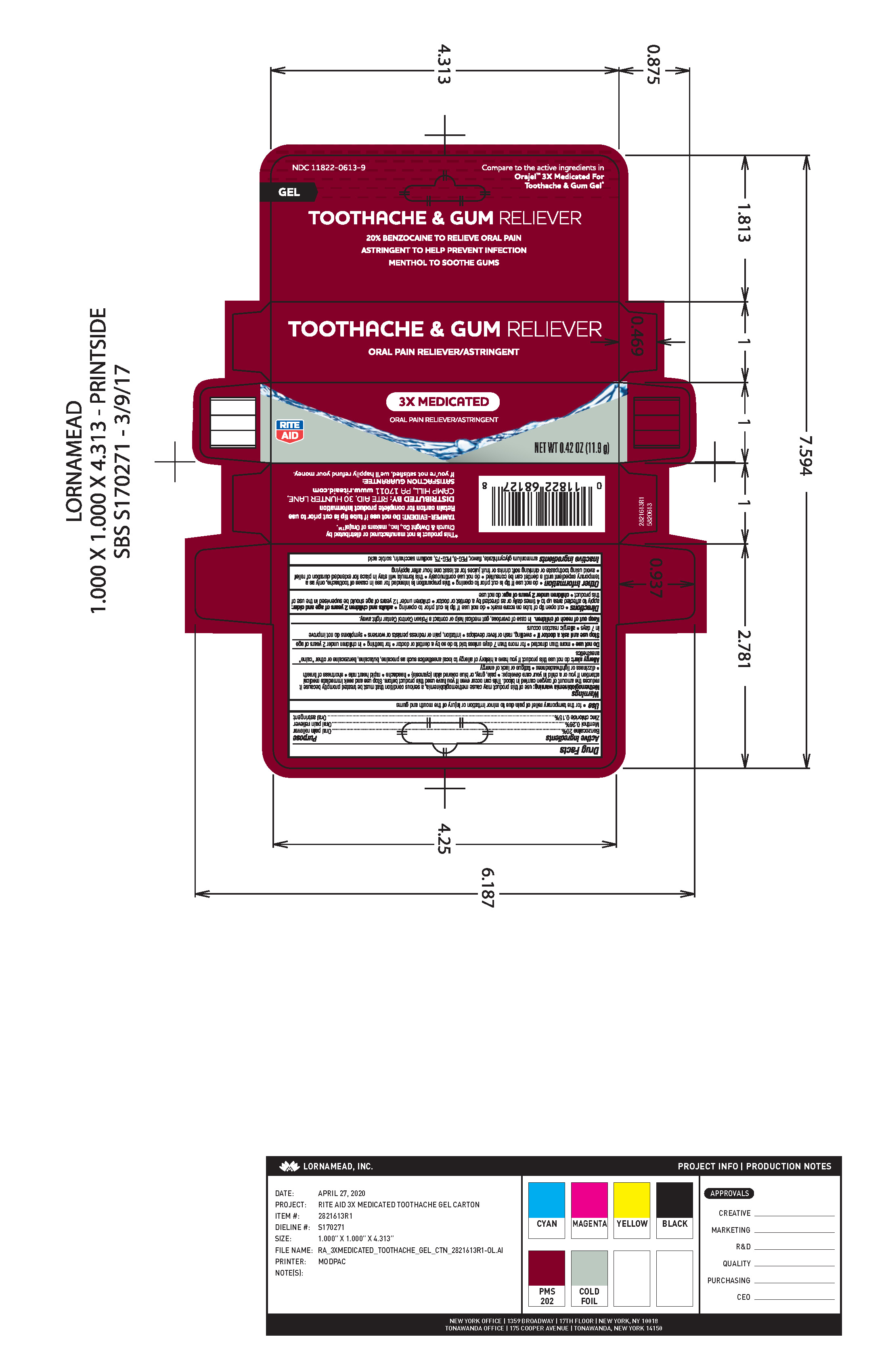 DRUG LABEL: 3X Medicated Toothache and Gum Gel
NDC: 11822-0613 | Form: GEL
Manufacturer: Rite Aid
Category: otc | Type: HUMAN OTC DRUG LABEL
Date: 20260106

ACTIVE INGREDIENTS: BENZOCAINE 20 g/100 g; MENTHOL 0.26 g/100 g; ZINC CHLORIDE 0.15 g/100 g
INACTIVE INGREDIENTS: POLYETHYLENE GLYCOL 3350; SACCHARIN SODIUM; POLYETHYLENE GLYCOL 400; SORBIC ACID; AMMONIUM GLYCYRRHIZATE

ACTIVE INGREDIENT

Acive Ingredients Purpose

Benzocaine 20% .......... Oral Pain Reliever

Menthol 0.26% ............. Oral Pain Reliever

Zinc Chloride 0.15% .... Oral Astringent

Use

Use * for the temporary relief of pain due to minor irritation or injury of the mouth and gums

INDICATIONS AND USAGE

Methemoglobinemia warning: use of this product may cause methemoglobinema, a serious condition that must be treated promptly because it reduces the amount of oxygen in the blood. This can occur even if you have used this prouct before. Stop use and seek immediate medical attention if you or a child in your care develops: * pale, gray, or blue colored skin (cyanosis) * headache * rapid heart rate * shortness of breath * dizziness or lightheadedness * fatigue or lack of energy

Allergy Alert

do not use this product if you have a history of allergy to local anesthetics such as procaine, butacaine, benzocaine or other "caine" anesthetics

Do not use * more than directed * for more than 7 days unless told to do so by a dentist or doctor * for teething * in children under 2 years of age

Stop use and ask a doctor if * swelling, rash or fever develops * irritation, pain or redness persists or worsens * symptoms do not improve in 7 days * allergic reaction occurs

Keep out of reach of children In case of overdose, get medical help or contact a Poison Control Center right away.

Directions

Directions * cut open tip of tube on score mark * do not use if tip is cut prior to opening * adults adn children 2 years of age and older: apply to affected area up to 4 times daily or as directed by a dentist or doctor * children under 12 years of age should be supervised in the use of this product * children under 2 years of age: do not use

Other information * do not use if tip is cut prior to opening * this preparation is intended for use in cases of toothache, only as a temporary expedient until a dentist can be consulted * do not use continuously (this formula will stay in place for extended duration of relief * avoid using toothpaste or drinking soft drinks or fruit juices for at least one hour after applying

INACTIVE INGREDIENT

Inactive ingredients ammonium glycyrrhizate, favor, PEG-8, PEG-75, sodium saccharin, sorbic acid

PACKAGE LABEL

Toothache and Gum Reliever

20% benzocaine to relive oral pain

Astringent to help prevent infection

Menthol to soothe gums

3x medicated

oral pain reliever/astringent

Net Wt 0.42 oz (11.9 g)